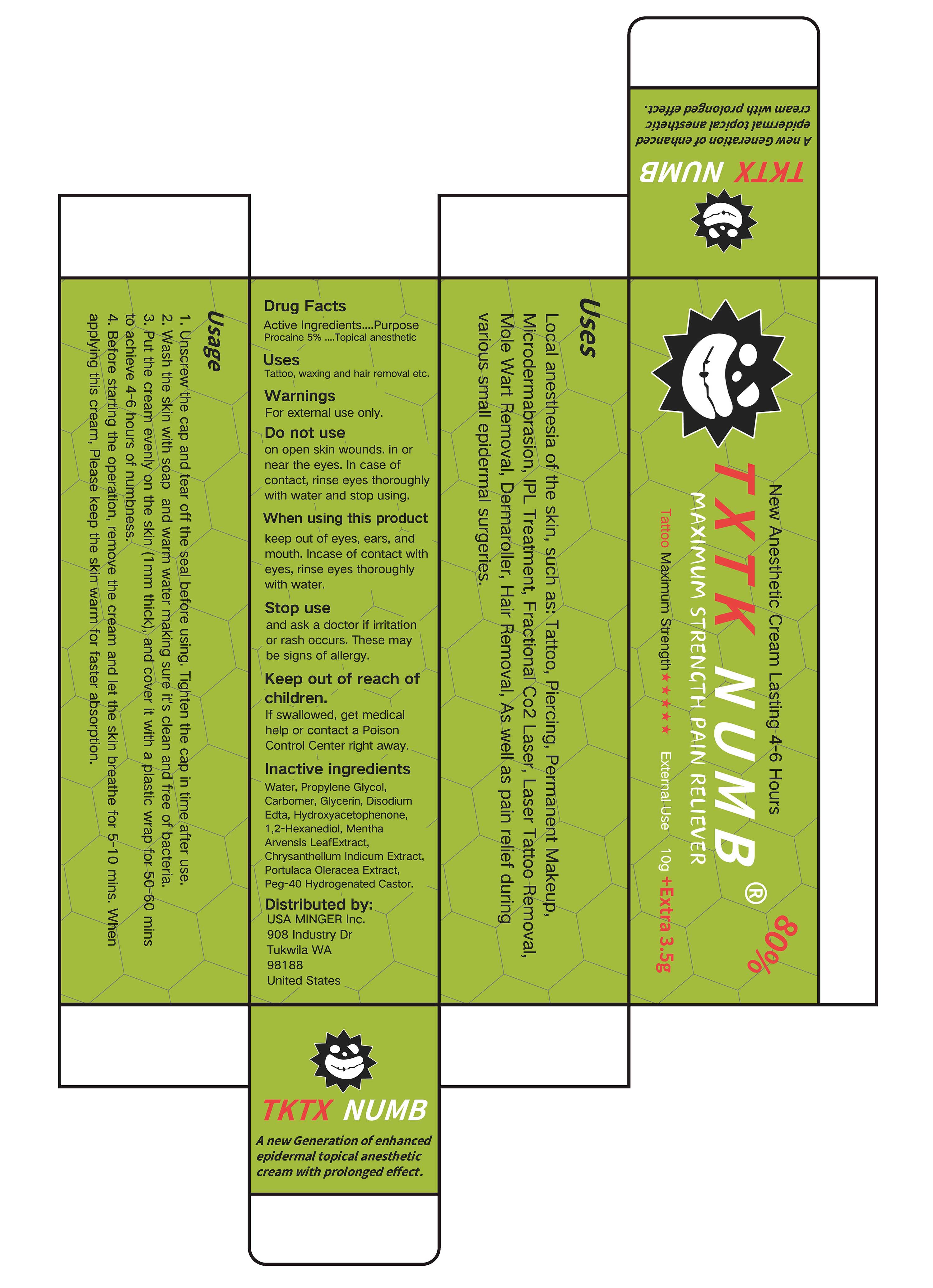 DRUG LABEL: TXTK NUMB
NDC: 84353-003 | Form: OINTMENT
Manufacturer: USA MINGER Inc.
Category: otc | Type: HUMAN OTC DRUG LABEL
Date: 20250314

ACTIVE INGREDIENTS: PROCAINE 0.05 g/1 g
INACTIVE INGREDIENTS: PROPYLENE GLYCOL; 1,2-HEXANEDIOL; HYDROXYACETOPHENONE; AQUA; MENTHA ARVENSIS LEAF; CARBOMER; CHRYSANTHELLUM INDICUM TOP; GLYCERIN; PURSLANE; EDETATE DISODIUM; PEG-40 HYDROGENATED CASTOR OIL

TXTK NUMB

ACTIVE INGREDIENT

Procaine 5%

PURPOSE

Topical anesthetic

INDICATIONS AND USAGE

Tattoo, waxing and hair removal etc.

WARNINGS

For external use only.

DO NOT USE

on open skin wounds.in ornear the eyes. In case ofcontact, rinse eyes thoroughlywith water and stop using.

WHEN USING

keep out of eyes, ears, andmouth.Incase of contact witheyes, rinse eyes thoroughlywith water.

STOP USE

and ask a doctor if irritationor rash occurs. These maybe signs of allergy.

KEEP OUT OF REACH OF CHILDREN

If swallowed, get medicalhelp or contact a PoisonControl Center right away.

DOSAGE AND ADMINISTRATION

1. Unscrew the cap and tear off the seal before using. Tighten the cap in time after use.
2. Wash the skin with soap and warm water making sure it's clean and free of bacteria
3. Put the cream evenly on the skin/(1 mm thick), and cover it with a plastic wrap for 50-60 minsto achieve 4-6 hours of numbness.
4. Before starting the operation, remove the cream and let the skin breathe for 5-10 mins. Whenapplying this cream, Please keep the skin warm for faster absorption.

INACTIVE INGREDIENT

AQUA
1,2-HEXANEDIOL
PROPYLENE GLYCOL
MENTHA ARVENSIS LEAF EXTRACT
CARBOMER
CHRYSANTHELLUM INDICUM EXTRACT
GLYCERIN
PORTULACA OLERACEA EXTRACT
DISODIUM EDTA
PEG-40 HYDROGENATED CASTOR
HYDROXYACETOPHENONE